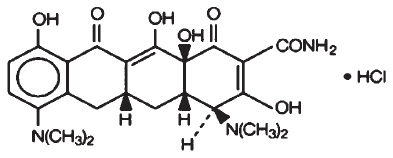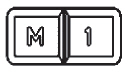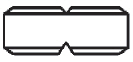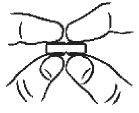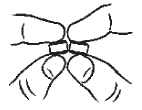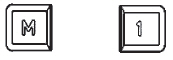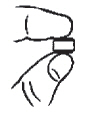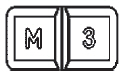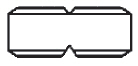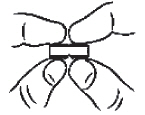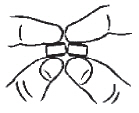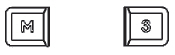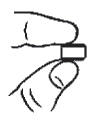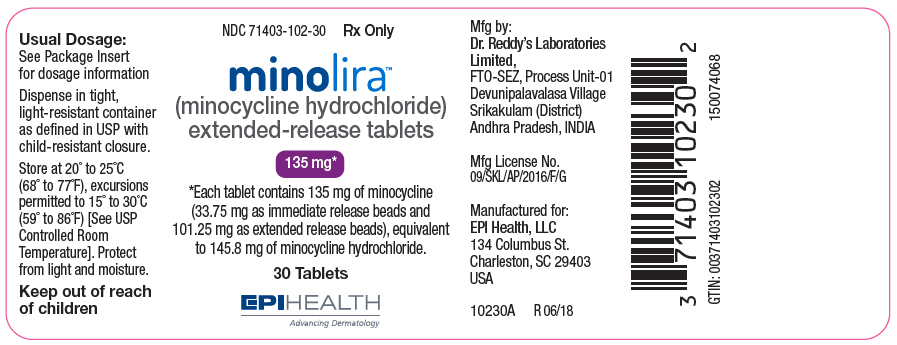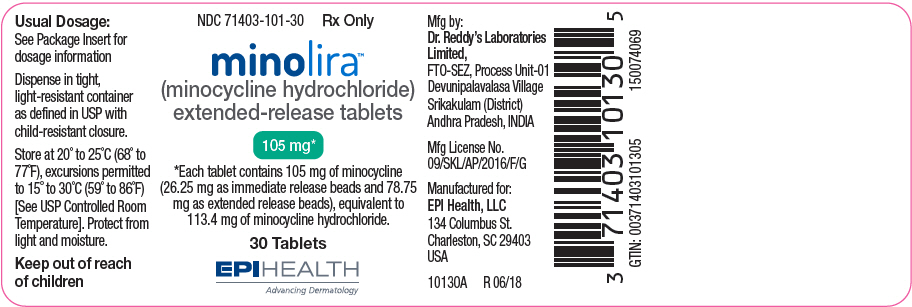 DRUG LABEL: Minolira Extended Release
NDC: 71403-102 | Form: TABLET
Manufacturer: EPI Health, Inc
Category: prescription | Type: HUMAN PRESCRIPTION DRUG LABEL
Date: 20221102

ACTIVE INGREDIENTS: Minocycline Hydrochloride 135 mg/1 1
INACTIVE INGREDIENTS: Isopropyl Alcohol; Sodium Stearyl Fumarate; Talc; MICROCRYSTALLINE CELLULOSE; Hypromellose 2910 (5 Mpa.S); Polyethylene Glycol 400; Ethylcellulose (10 Mpa.S); Hypromellose 2910 (15 Mpa.S); Triethyl Citrate; HYDROXYPROPYL CELLULOSE (1600000 WAMW); Water

HIGHLIGHTS OF PRESCRIBING INFORMATION

These highlights do not include all the information needed to use MINOLIRA™ safely and effectively. See full prescribing information for MINOLIRA.
MINOLIRA™ (minocycline hydrochloride) extended-release tablets, for oral use
Initial U.S. Approval: 1971

1 INDICATIONS AND USAGE

MINOLIRA is a tetracycline-class drug indicated to treat only inflammatory lesions of non-nodular moderate to severe acne vulgaris in patients 12 years of age and older. (1)

Limitations of Use

This formulation of minocycline has not been evaluated in the treatment of infections. To reduce the development of drug-resistant bacteria as well as to maintain the effectiveness of other antibacterial drugs, MINOLIRA should be used only as indicated [see Warnings and Precautions (5.13)].

2 DOSAGE AND ADMINISTRATION

Recommended dosage: Approximately 1 mg/kg once daily for 12 weeks. (2)

3 DOSAGE FORMS AND STRENGTHS

Extended- release tablets: 105 mg and 135 mg of minocycline, functionally scored (3)

4 CONTRAINDICATIONS

This drug is contraindicated in persons who have shown hypersensitivity to any of the tetracyclines. (4)

5 WARNINGS AND PRECAUTIONS

- The use of MINOLIRA during the second and third trimesters of pregnancy, infancy and childhood up to the age of 8 years may cause permanent discoloration of the teeth (yellow-gray-brown) and reversible inhibition of bone growth. (5.1, 5.2, 5.3, 8.1, 8.4)
- If pseudomembranous colitis occurs, discontinue MINOLIRA. (5.4)
- If liver injury is suspected, discontinue MINOLIRA. (5.5)
- If renal impairment exists, MINOLIRA doses may need to be adjusted to avoid excessive systemic accumulations of the drug and possible liver toxicity. (5.6)
- Minocycline may cause central nervous system side effects including lightheadedness, dizziness, or vertigo. (5.7)
- Minocycline may cause intracranial hypertension in adults and adolescents. Discontinue MINOLIRA if symptoms occur. (5.8)
- Minocycline has been associated with autoimmune syndromes; discontinue MINOLIRA immediately if symptoms occur. (5.9)
- Minocycline has been associated with anaphylaxis, serious skin reactions, erythema multiforme, and DRESS syndrome. Discontinue MINOLIRA immediately if symptoms occur. (5.11)

6 ADVERSE REACTIONS

The most commonly observed adverse reactions (incidence ≥5%) are headache, fatigue, dizziness, and pruritus. (6.1)

To report SUSPECTED ADVERSE REACTIONS, contact EPI Health, LLC at 1-800-499-4468 or www.epihealth.com or FDA at 1-800-FDA-1088 or www.fda.gov/medwatch.

7 DRUG INTERACTIONS

- Patients who are on anticoagulant therapy may require downward adjustment of their anticoagulant dosage. (7.1)
- To avoid contraceptive failure, female patients are advised to use a second form of contraception during treatment with minocycline. (7.4)

8 USE IN SPECIFIC POPULATIONS

- Minocycline like other tetracycline-class drugs can cause fetal harm when administered to a pregnant woman.
- The use of drugs of the tetracycline class during tooth development may cause permanent discoloration of teeth. (5.1, 5.2, 8.1, 8.4)
- Lactation: Breastfeeding is not recommended. (8.2)

FULL PRESCRIBING INFORMATION

1 INDICATIONS AND USAGE

MINOLIRA is indicated to treat the inflammatory lesions of non-nodular moderate to severe acne vulgaris in patients 12 years of age and older.

Limitations of Use

This formulation of minocycline has not been evaluated in the treatment of infections.

To reduce the development of drug-resistant bacteria as well as to maintain the effectiveness of other antibacterial drugs, MINOLIRA should be used only as indicated [see Warnings and Precautions (5.13)].

2 DOSAGE AND ADMINISTRATION

The recommended dosage of MINOLIRA is approximately 1 mg/kg once daily for 12 weeks. Higher doses have not shown to be of additional benefit in the treatment of inflammatory lesions of acne, and may be associated with more acute vestibular side effects. The 105 mg and 135 mg tablets may be split on the score line for dosing of patient weight ranges of 45-59 kg and 60-89 kg, respectively (see Table 1).

Table 1: Dosing Table for MINOLIRA
Patient's Weight (kg) | Daily Dose | Tablet Strength and Size to Administer | Actual Dose (mg/kg)
45 – 59 | 52.5 | half of the 105 mg tablet | 1.16 –0.88
60 – 89 | 67.5 | half of the 135 mg tablet | 1.13 – 0.76
90 – 125 | 105 | one 105 mg tablet | 1.17 – 0.84
126 – 136 | 135 | one 135 mg tablet | 1.07 – 0.99

MINOLIRA may be taken with or without food [see Clinical Pharmacology (12.3)]. Ingestion of food along with MINOLIRA may help reduce the risk of esophageal irritation and ulceration. MINOLIRA tablets should not be chewed or crushed.

In patients with renal impairment, the total dosage should be decreased by either reducing the recommended individual doses and/or by extending the time intervals between doses [see Warnings and Precautions (5.6)].

3 DOSAGE FORMS AND STRENGTHS

MINOLIRA extended-release tablets are white to off-white, functionally scored, rectangular tablets with brown or gold color speckles and a single score line on both surfaces. MINOLIRA are available in the following two strengths.

- 105 mg extended-release tablets: ‘M1’debossed on one surface, where ‘M’ and ‘1’ are on either side of the score line. Each tablet contains 105 mg minocycline, equivalent to 113.4 mg of minocycline hydrochloride.
- 135 mg extended-release tablets: ‘M3’ is debossed on one surface, where ‘M’ and ‘3’ are on either side of the score line. Each tablet contains 135 mg minocycline, equivalent to 145.8 mg of minocycline hydrochloride.

4 CONTRAINDICATIONS

MINOLIRA is contraindicated in patients who have shown hypersensitivity to any of the tetracyclines [see Serious Skin/Hypersensitivity Reactions (5.11)].

5 WARNINGS AND PRECAUTIONS

5.1 Teratogenic Effects

Avoid MINOLIRA use during pregnancy.

MINOLIRA, like other tetracycline-class drugs, can cause fetal harm when administered to a pregnant woman. MINOLIRA, like other tetracycline-class drugs, may cause permanent discoloration of the teeth and inhibit bone growth when administered during pregnancy. Based on animal data, tetracyclines cross the placenta, are found in fetal tissues, and can cause skeletal malformation and retardation of skeletal development on the developing fetus. Evidence of embryotoxicity has been noted in animals treated early in pregnancy. If MINOLIRA is used during pregnancy, advise the patient of the potential risk to the fetus and discontinue treatment [see Use in Specific Populations (8.1)].

5.2 Tooth Discoloration

The use of tetracycline class drugs during tooth development (second and third trimesters of pregnancy, infancy, and childhood up to the age of 8 years) may cause permanent discoloration of the teeth (yellow-gray-brown). This adverse reaction is more common during long-term use of the tetracycline but has been observed following repeated short-term courses. Enamel hypoplasia has also been reported. Use of tetracycline drugs is not recommended during tooth development.

The safety and effectiveness of MINOLIRA have not been established in pediatric patients less than 12 years of age.

5.3 Inhibition of Bone Growth

All tetracyclines form a stable calcium complex in any bone-forming tissue. A decrease in fibula growth rate has been observed in premature human infants given oral tetracycline in doses of 25 mg/kg every 6 hours. This reaction was shown to be reversible when the drug was discontinued. The safety and effectiveness of MINOLIRA have not been established in patients less than 12 years of age [see Use in Specific Populations (8.1, 8.4)].

Results of animal studies indicate that tetracyclines cross the placenta, are found in fetal tissues, and can cause retardation of skeletal development on the developing fetus. Evidence of embryotoxicity has been noted in animals treated early in pregnancy [see Use in Specific Populations (8.1)].

5.4 Pseudomembranous Colitis

Clostridium difficile associated diarrhea (CDAD) has been reported with nearly all antibacterial agents, including minocycline, and may range in severity from mild diarrhea to fatal colitis. Treatment with antibacterial agents alters the normal flora of the colon leading to overgrowth of C. difficile.

C. difficile produces toxins A and B which contribute to the development of CDAD. Hypertoxin producing strains of C. difficile cause increased morbidity and mortality, as these infections can be refractory to antimicrobial therapy and may require colectomy. CDAD must be considered in all patients who present with diarrhea following antibiotic use. Careful medical history is necessary since CDAD has been reported to occur over two months after the administration of antibacterial agents.

If CDAD is suspected or confirmed, antibiotic use not directed against C. difficile may need to be discontinued. Appropriate fluid and electrolyte management, protein supplementation, antibiotic treatment of C. difficile, and surgical evaluation should be instituted as clinically indicated.

5.5 Hepatotoxicity

Post-marketing cases of serious liver injury, including irreversible drug-induced hepatitis and fulminant hepatic failure (sometimes fatal) have been reported with minocycline use in the treatment of acne.

5.6 Metabolic Effects

The anti-anabolic action of the tetracyclines may cause an increase in BUN. While this is not a problem in those with normal renal function, in patients with significantly impaired function, higher serum levels of tetracycline-class drugs may lead to azotemia, hyperphosphatemia, and acidosis. If renal impairment exists, even usual oral or parenteral doses may lead to excessive systemic accumulations of the drug and possible liver toxicity. Under such conditions, lower than usual total doses are indicated, and if therapy is prolonged, serum level determinations of the drug may be advisable.

5.7 Central Nervous System Effects

Central nervous system side effects including light-headedness, dizziness or vertigo have been reported with minocycline therapy. Patients who experience these symptoms should be cautioned about driving vehicles or using hazardous machinery while on minocycline therapy. These symptoms may disappear during therapy and usually rapidly disappear when the drug is discontinued.

5.8 Intracranial Hypertension

Intracranial hypertension has been associated with the use of tetracycline-class drugs including MINOLIRA. Clinical manifestations of intracranial hypertension include headache, blurred vision, diplopia and vision loss; papilledema can be found on fundoscopy. Women of childbearing age who are overweight or have a history of IH are at a greater risk for developing intracranial hypertension. Concomitant use of isotretinoin and tetracycline should be avoided because isotretinoin, a systemic retinoid, is also known to cause intracranial hypertension.

Although intracranial hypertension typically resolves after discontinuation of treatment, the possibility for permanent visual loss exists. If visual disturbance occurs during treatment, prompt ophthalmologic evaluation is warranted. Because intracranial pressure can remain elevated for weeks after drug cessation, patients should be monitored until they stabilize.

5.9 Autoimmune Syndromes

Tetracyclines have been associated with the development of autoimmune syndromes. The long- term use of minocycline in the treatment of acne has been associated with drug-induced lupus- like syndrome, autoimmune hepatitis and vasculitis. Sporadic cases of serum sickness have presented shortly after minocycline use. Symptoms may be manifested by fever, rash, arthralgia, and malaise. In symptomatic patients, immediately discontinue the use of all tetracycline-class drugs, including MINOLIRA.

5.10 Photosensitivity

Photosensitivity manifested by an exaggerated sunburn reaction has been observed in some individuals taking tetracyclines; this reaction has been reported less frequently with minocycline. Patients should minimize or avoid exposure to natural or artificial sunlight (tanning beds or UVA/B treatment) while using minocycline. If patients need to be outdoors while using MINOLIRA, they should wear loose-fitting clothes that protect skin from sun exposure and discuss other sun protection measures with their physician.

5.11 Serious Skin/Hypersensitivity Reaction

Cases of anaphylaxis, serious skin reactions (e.g. Stevens Johnson syndrome), erythema multiforme, and drug reaction with eosinophilia and systemic symptoms (DRESS) syndrome have been reported postmarketing with minocycline use in patients with acne. DRESS syndrome consists of cutaneous reaction (such as rash or exfoliative dermatitis), eosinophilia, and one or more of the following visceral complications such as: hepatitis, pneumonitis, nephritis, myocarditis, and pericarditis. Fever and lymphadenopathy may be present. In some cases, death has been reported. If this syndrome is recognized, discontinue MINOLIRA immediately.

5.12 Tissue Hyperpigmentation

Tetracyclines are known to cause hyperpigmentation. Tetracycline therapy may induce hyperpigmentation in many organs, including nails, bone, skin, eyes, thyroid, visceral tissue, oral cavity (teeth, mucosa, alveolar bone), sclerae and heart valves. Skin and oral pigmentation has been reported to occur independently of time or amount of drug administration, whereas other tissue pigmentation has been reported to occur upon prolonged administration. Skin pigmentation includes diffuse pigmentation as well as pigmentation over sites of scars or injury.

5.13 Development of Drug-Resistant Bacteria

MINOLIRA has not been evaluated in the treatment of infections.

Bacterial resistance to the tetracyclines may develop in patients using MINOLIRA. Because of the potential for drug-resistant bacteria to develop during the use of MINOLIRA, it should be used only as indicated.

5.14 Superinfection

Use of MINOLIRA may result in overgrowth of nonsusceptible organisms, including fungi. If super infection occurs, discontinue MINOLIRA and institute appropriate therapy.

5.15 Laboratory Monitoring

Periodic laboratory evaluations of organ systems, including hematopoietic, renal and hepatic studies should be performed. Appropriate tests for autoimmune syndromes should be performed as indicated.

6 ADVERSE REACTIONS

6.1 Clinical Trials Experience

Because clinical trials are conducted under widely varying conditions, adverse reaction rates observed in the clinical trials of a drug cannot be directly compared to rates in the clinical trials of another drug, and may not reflect the rates observed in practice.

The following table summarizes selected adverse reactions reported in clinical trials at a rate of ≥1% for minocycline hydrochloride extended release tablets.

Table 2: Selected Treatment-Emergent Adverse Reactions in at least 1% of Clinical Trial
Adverse Reactions | Minocycline Hydrochloride Extended-Release Tablets (1 mg/kg) N = 674 (%) | Placebo N = 364 (%)
At least one treatment emergency event | 379 (56) | 197 (54)
Headache | 152(23) | 83(23)
Fatigue | 62 (9) | 24 (7)
Dizziness | 59 (9) | 17 (5)
Pruritus | 31 (5) | 16 (4)
Malaise | 26 (4) | 9 (3)
Mood alteration | 17 (3) | 9 (3)
Somnolence | 13 (2) | 3 (1)
Urticaria | 10 (2) | 1 (0)
Tinnitus | 10 (2) | 5 (1)
Arthralgia | 9 (1) | 2 (0)
Vertigo | 8 (1) | 3 (1)
Dry Mouth | 7 (1) | 5 (1)
Myalgia | 7 (1) | 4 (1)

6.2 Postmarketing Experience

Adverse reactions that have been reported with minocycline hydrochloride use in a variety of indications include:

Skin and hypersensitivity reactions: fixed drug eruptions, balanitis, erythema multiforme, Stevens-Johnson syndrome, anaphylactoid purpura, photosensitivity, pigmentation of skin and mucous membranes, hypersensitivity reactions, angioneurotic edema, anaphylaxis, DRESS syndrome [see Warnings and Precautions (5.11)].

Autoimmune conditions: polyarthralgia, pericarditis, exacerbation of systemic lupus, pulmonary infiltrates with eosinophilia, transient lupus-like syndrome.

Central nervous system: pseudotumor cerebri, bulging fontanels in infants, decreased hearing.

Endocrine: brown-black microscopic thyroid discoloration, abnormal thyroid function.

Oncology: thyroid cancer.

Oral: glossitis, dysphagia, tooth discoloration.

Gastrointestinal: enterocolitis, pancreatitis, hepatitis, liver failure.

Genitourinary: Preliminary studies suggest that use of minocycline may have deleterious effects on human spermatogenesis [see Nonclinical Toxicoloty (13.1)].

Renal: reversible acute renal failure.

Hematology: hemolytic anemia, thrombocytopenia, eosinophilia.

7 DRUG INTERACTIONS

7.1 Anticoagulants

Because tetracyclines have been shown to depress plasma prothrombin activity, patients who are on anticoagulant therapy may require downward adjustment of their anticoagulant dosage.

7.2 Penicillin

Because bacteriostatic drugs may interfere with the bactericidal action of penicillin, to avoid giving tetracycline-class drugs in conjunction with penicillin.

7.3 Antacids and Iron Preparations

Absorption of tetracyclines is impaired by antacids containing aluminum, calcium or magnesium and iron-containing preparations.

7.4 Low Dose Oral Contraceptives

In a multi-center study to evaluate the effect of minocycline extended release tablets on low dose oral contraceptives, hormone levels over one menstrual cycle with and without minocycline extended release tablets 1 mg/kg once-daily were measured. Based on the results of this trial, minocycline-related changes in estradiol, progestinic hormone, FSH and LH plasma levels, of breakthrough bleeding, or of contraceptive failure, cannot be ruled out. To avoid contraceptive failure during treatment with minocycline, advise patients of reproductive potential to use a second form of contraception in addition to low-dose oral contraceptives.

7.5 Drug/Laboratory Test Interactions

False elevations of urinary catecholamine levels may occur due to interference with the fluorescence test.

8 USE IN SPECIFIC POPULATIONS

8.1 Pregnancy

Risk Summary

MINOLIRA, like tetracycline class drugs, may cause permanent discoloration of teeth and reversible inhibition of bone growth when administered during pregnancy [see Warnings and Precautions (5.1) and Use in Specific Populations (8.4)]. Post-marketing cases of minocycline use in pregnant women report congenital anomalies such as limb reductions. The limited data are not sufficient to inform a drug-associated risk for birth defects or miscarriage. In animal reproduction studies, minocycline induced skeletal malformations in fetuses when orally administered to pregnant rats and rabbits during the period of organogenesis at systemic exposure of approximately 3 times and 2 times, respectively, the systemic exposure to minocycline observed in patients administered MINOLIRA (see Data). If a patient becomes pregnant while taking this drug, advise the patient of the risk to the fetus and discontinue treatment.

The estimated background risk of major birth defects and miscarriage for the indicated population is unknown. All pregnancies have a background risk of birth defect, loss, or other adverse outcomes. In the U.S. general population, the estimated background risk of major birth defects and miscarriage in clinically recognized pregnancies is 2-4% and 15-20%, respectively.

Data

Human Data

The use of tetracycline during tooth development (second and third trimesters of pregnancy) may cause permanent discoloration of deciduous teeth. This adverse reaction is more common during long-term use of the drug but has been observed following repeated short-term courses.

Animal Data

Results of animal studies indicate that tetracyclines cross the placenta, are found in fetal tissues, and can cause retardation of skeletal development of the developing fetus. [see Warnings and Precautions (5.1)].

Minocycline induced skeletal malformations (bent limb bones) in fetuses when administered to pregnant rats and rabbits during the period of organogenesis at doses of 30 mg/kg/day and 100 mg/kg/day, respectively, (resulting in approximately 3 times and 2 times, respectively, the systemic exposure to minocycline observed in patients administered MINOLIRA). Reduced mean fetal body weight was observed when minocycline was administered to pregnant rats during the period of organogenesis at a dose of 10 mg/kg/day (which resulted in approximately the same level of systemic exposure to minocycline as that observed in patients administered MINOLIRA).

Minocycline was assessed for effects on peri- and post-natal development of rats in a study that involved oral administration to pregnant rats during the period of organogenesis through lactation , at doses of 5, 10, or 50 mg/kg/day. In this study, body weight gain was significantly reduced in pregnant females that received 50 mg/kg/day (resulting in approximately 2.5 times the systemic exposure to minocycline observed in patients administered MINOLIRA). No effects of treatment on the duration of the gestation period or the number of live pups born per litter were observed. Gross external anomalies observed in F1 pups (offspring of animals that received minocycline) included reduced body size, improperly rotated forelimbs, and reduced size of extremites. No effects were observed on the physical development, behavior, learning ability, or reproduction of F1 pups, and there was no effect on gross appearance of F2 pups (offspring of F1 animals).

8.2 Lactation

Risk Summary

Tetracycline-class drugs including minocycline are present in breast milk. It is not known whether minocycline has an effect on the breastfed infant or on milk production. Because of the potential for serious adverse effects on bone and tooth development in breastfed infants from the tetracycline-class drugs, advise a woman that breastfeeding is not recommended with MINOLIRA therapy [see Warnings and Precautions (5.1)].

8.3 Females and Males of Reproductive Potential

Contraception

MINOLIRA may reduce the effectiveness of low-dose oral contraceptives. Patients of reproductive potential should not rely on low-dose oral contraceptives as an effective contraceptive method, and should use an additional method of contraception during treatment with MINOLIRA [see Drug Interactions (7.4)].

Infertility

Avoid using MINOLIRA in males who are attempting to conceive a child. Limited human studies suggest that minocycline may have a deleterious effect on spermatogenesis. In a fertility study in rats, minocycline adversely affected spermatogenesis when orally administered to male rats at doses resulting in approximately 15 to 40 times the level of systemic exposure to minocycline observed in patients administered MINOLIRA [see Nonclinical Toxicology (13.1)].

8.4 Pediatric Use

The safety and effectiveness of MINOLIRA have been established in pediatric patients 12 years of age and older for the treatment of inflammatory lesions of non-nodular moderate to severe acne vulgaris [see Pharmacokinetics (12.3) and Clinical Studies (14)]. Tooth discoloration and inhibition of bone growth have been observed in pediatric patients [see Warnings and Precautions (5.2, 5.3)]. The safety and effectiveness of MINOLIRA have not been established in pediatric patients less than 12 years of age.

8.5 Geriatric Use

Clinical studies of MINOLIRA did not include sufficient numbers of subjects aged 65 years and over to determine whether they respond differently from younger subjects. Other reported clinical experience has not identified differences in responses between the elderly and younger patients.

In general, dose selection for an elderly patient should be cautious, usually starting at the low end of the dosing range, reflecting the greater frequency of decreased hepatic, renal, or cardiac function, and concomitant disease or other drug therapy.

10 OVERDOSAGE

In case of over dosage, discontinue medication, treat symptomatically and institute supportive measures. Minocycline is not removed in significant quantities by hemodialysis or peritoneal dialysis.

11 DESCRIPTION

Minocycline hydrochloride, a semi synthetic derivative of tetracycline, is [4S (4α,4aα,5aα,12aα)]-4,7-Bis(dimethylamino)-1,4,4a,5,5a,6,11,12a-octahydro-3,10,12,12a tetrahydroxy-1,11-dioxo-2-naphthacenecarboxamide mono hydrochloride. The structural formula is representated below:

C23H27N3O7∙HCl M. W. 493.95

MINOLIRA (minocycline hydrochloride) extended-release tablets for oral administration contain 105 mg or 135 mg of minocycline, equivalent to 113.4 mg or 145.8 mg of minocycline hydrochloride, respectively. MINOLIRA extended-release tablets, 105 mg and 135 mg, contain 25% of minocycline as immediate release beads and 75% of minocycline as extended release beads.

In addition, 105 mg and 135 mg tablets contain the following inactive ingredients: ethyl cellulose NF, hypromellose USP, isopropyl alcohol USP, microcrystalline cellulose NF, polytheylene glycol 400 NF, purified water USP, silicified microcrystalline cellulose NF, sodium stearyl fumarate NF, talc USP, triethyl citrate NF.

Both 105 mg and 135 mg tablets also contain Opadry clear which contains hydroxyl propyl cellulose NF and hypromellose USP.

12 CLINICAL PHARMACOLOGY

12.1 Mechanism of Action

The mechanism of action of MINOLIRA for the treatment of acne is unknown.

12.2 Pharmacodynamics

The pharmacodynamics of MINOLIRA for the treatment of acne are unknown.

12.3 Pharmacokinetics

The pharmacokinetics of minocycline following oral administration of a single dose of MINOLIRA (135 mg) was investigated in 77 healthy male and female adult subjects under fasting conditions. The pharmacokinetic parameters of minocycline under fasting conditions are presented in Table 3.

Table 3 : Pharmacokinetic Parameters of Minocycline Following Administration of a Single Dose of MINOLIRA (135 mg) under Fasting Conditions (N = 77)
 | Cmax (ng/mL) | Tmax (hr) [Median (Min-Max)] | AUC0-t (ng∙hr/mL) | T1/2 (hr)
Mean ± SD | 700 ± 261 | 2.0 (1.0 – 4.5) | 10874 ± 3717 | 15.6 ± 2.46

In a separate trial, a single dose of MINOLIRA (135 mg) was administered orally with a high-fat, high-calorie meal that included dairy products to 36 healthy male and female adult subjects. The estimated calorie content of the meal was 848 Kcal, consisting of 145 Kcal from protein, 250 Kcal from carbohydrates, and 453 Kcal from fat. The pharmacokinetic parameters of minocycline under fed conditions are presented in Table 4.

Table 4 : Pharmacokinetic Parameters of Minocycline Following Administration of a Single Dose of MINOLIRA (135 mg) under Fed Conditions (N = 36)
 | Cmax (ng/mL) | Tmax (hr) [Median (Min-Max)] | AUC0-t (ng∙hr/mL) | T1/2 (hr)
Mean ± SD | 707 ± 190 | 3.5 (1.5 – 6.0) | 12000 ± 2967 | 17.1 ± 3.03

Minocycline is lipid soluble and distributes into the skin and sebum.

13 NONCLINICAL TOXICOLOGY

13.1 Carcinogenesis, Mutagenesis, Impairment of Fertility

In a carcinogenicity study in which minocycline hydrochloride was orally administered to male and female rats once daily for up to 104 weeks at dosages up to 200 mg/kg/day, minocycline hydrochloride was associated in both genders with follicular cell tumors of the thyroid gland, including increased incidences of adenomas, carcinomas, and the combined incidence of adenomas and carcinomas in males, and adenomas and the combined incidence of adenomas and carcinomas in females. In a carcinogenicity study in which minocycline hydrochloride was orally administered to male and female mice once daily for up to 104 weeks at dosages up to 150 mg/kg/day, exposure to minocycline hydrochloride did not result in a significantly increased incidence of neoplasms in either males or females.

Minocycline was not mutagenic in vitro in a bacterial reverse mutation assay (Ames test) or CHO/HGPRT mammalian cell assay in the presence or absence of metabolic activation. Minocycline was not clastogenic in vitro using human peripheral blood lymphocytes or in vivo in a mouse micronucleus test.

Male and female reproductive performance in rats was unaffected by oral doses of minocycline of up to 300 mg/kg/day (which resulted in up to approximately 40 times the level of systemic exposure to minocycline observed in patients administered MINOLIRA). However, oral administration of 100 or 300 mg/kg/day of minocycline to male rats (resulting in approximately 15 to 40 times the level of systemic exposure to minocycline observed in patients administered MINOLIRA) adversely affected spermatogenesis. Effects observed at 300 mg/kg/day included a reduced number of sperm cells per gram of epididymis, an apparent reduction in the percentage of sperm that were motile, and (at 100 and 300 mg/kg/day) increased numbers of morphologically abnormal sperm cells. Morphological abnormalities observed in sperm samples included absent heads, misshapen heads, and abnormal flagella.

14 CLINICAL STUDIES

The safety and efficacy of minocycline hydrochloride extended-release tablets in the treatment of inflammatory lesions of non-nodular moderate to severe acne vulgaris was assessed in two 12-week, multi-center, randomized, double-blind, placebo-controlled, trials in subjects ≥12 years. The mean age of subjects was 20 years and subjects were from the following racial groups: White (73%), Hispanic (13%), Black (11%), Asian/Pacific Islander (2%), and Other (2%).

In two efficacy and safety trials, a total of 924 subjects with non-nodular moderate to severe acne vulgaris received minocycline hydrochloride extended-release tablets (approximately 1 mg/kg) or placebo for a total of 12 weeks.

The two primary efficacy endpoints were:

1) Mean percent change in inflammatory lesion counts from Baseline to 12 weeks.

2) Percentage of subjects with an Evaluator's Global Severity Assessment (EGSA) of clear or almost clear at 12 weeks.

Efficacy results are presented in Table 5.

Table 5: Efficacy Results at Week 12
 | Trial 1 |  | Trial 2
 | Minocycline Hydrochloride Extended Release Tablets (1 mg/kg) N=300 | Placebo N=151 | Minocycline Hydrochloride Extended Release Tablets (1 mg/kg) N=315 | Placebo N=158
Mean Percent Improvement in Inflammatory Lesions | 43.1% | 31.7% | 45.8%
Number of subjects clear or almost clear on EGSA [Evaluator's Global Severity Assessment] | 52 (17.3%) | 12 (7.9%) | 50 (15.9%) | 15 (9.5%)

Minocycline hydrochloride did not demonstrate any effect on non-inflammatory lesions (benefit or worsening).

16 HOW SUPPLIED/STORAGE AND HANDLING

How Supplied

MINOLIRA is supplied as functionally scored extended-release tablets containing minocycline hydrochloride equivalent to 105 mg and 135 mg of minocycline.

The 105 mg extended-release tablets are white to off-white, rectangular, with brown or gold color speckles. The tablets have a single score line on both surfaces and are debossed with ‘M1’ on one surface. On the face with debossing, ‘M’ and ‘1’ are on either side of the score line. Each tablet contains 26.25 mg of minocycline as immediate release beads and 78.75 mg of minocycline as extended release beads. The 105 mg tablets are supplied as follows:

NDC 71403-101-30 | Bottle of 30

The 135 mg extended-release tablets are white to off-white, rectangular with brown or gold color speckles. The tablets have a single score line on both surfaces and are debossed with ‘M3’ on one surface. On the face with debossing, ‘M’ and ‘3’ are on either side of the score line. Each tablet contains 33.75 mg of minocycline as immediate release beads and 101.25 of minocycline as extended release beads. The 135 mg tablets are supplied as follows:

NDC 71403-102-30 | Bottle of 30

Storage

Store at 20°C - 25°C (68°F - 77°F); excursions are permitted to 15°C-30°C (59°-86°F) [see USP Controlled Room Temperature]. Protect from light and moisture.

Handling

Dispense in tight, light-resistant container as defined in USP with child-resistant closure.

17 PATIENT COUNSELING INFORMATION

Advise the patient to read the FDA-approved patient labeling (Patient Information and Instruction for Use).

Advise patients of the following:

Teratogenic effects

- Advise patients to avoid use of MINOLIRA during pregnancy.
- Advise patients that MINOLIRA use during pregnancy may cause inhibition of fetal bone growth.
- Advise patients that MINOLIRA use during pregnancy may cause discoloration of deciduous teeth.
- Advise patients to discontinue MINOLIRA during pregnancy.

Tooth Discoloration

- Advise caregivers of pediatric patients that MINOLIRA use may cause permanent discoloration of deciduous and permanent teeth.

Lactation

- Advise a woman that breast feeding is not recommended during MINOLIRA therapy.

Contraception

- Advise patients of reproductive potential that MINOLIRA may reduce the effectiveness of low-dose oral contraceptives. Advise patients of reproductive potential not rely on low-dose oral contraceptives as an effective contraceptive method and to use an additional method of contraception during treatment with MINOLIRA.

Infertility

- Advise males of reproductive potential that MINOLIRA may impair fertility.

Tissue Hyperpigmentation

- Inform patients that MINOLIRA may cause discoloration of skin, scars, teeth or gums.

Pseudomembranous Colitis

- Advise patients that pseudomembranous colitis can occur with minocycline therapy, including MINOLIRA. Advise patients to seek medical attention if they develop watery or bloody stools.

Hepatotoxicity

- Inform patients about the possibility of hepatotoxicity. Advise patients to seek medical advice if they experience symptoms or signs of hepatotoxicity, including loss of appetite, tiredness, diarrhea, jaundice, increased bleeding tendencies, confusion, and sleepiness.

Central Nervous System Effects

- Inform patients that central nervous system adverse reactions including dizziness or vertigo have been reported with minocycline therapy. Caution patients about driving vehicles or using hazardous machinery if they experience such symptoms while on MINOLIRA.

Intracranial Hypertension

- Inform patients that intracranial hypertension can occur with minocycline therapy. Advise patients to seek medical attention if they develop unusual headache, visual symptoms, such as blurred vision, diplopia, and vision loss.
- Inform patients that autoimmune syndromes, including drug-induced lupus-like syndrome, autoimmune hepatitis, vasculitis and serum sickness have been observed with tetracycline-class drugs, including minocycline. Symptoms may be manifested by arthralgia, fever, rash and malaise.
- Advise patients who experience such symptoms to stop the drug immediately and seek medical help.

Photosensitivity

- Inform patients that photosensitivity manifested by an exaggerated sunburn reaction has been observed in some individuals taking tetracyclines, including minocycline.
- Advise patients to minimize or avoid exposure to natural or artificial UV light (tanning beds or UVA/B treatment) while using MINOLIRA.
- Discuss other sun protection measures, if patients need to be outdoors while using MINOLIRA.
- Advise patients to discontinue treatment at the first evidence of sunburn.

Important Administration Instructions

- Inform patients to take MINOLIRA as directed. Missing doses or not completing the full course of therapy may decrease the effectiveness of the current treatment course and increase the likelihood that bacteria will develop resistance and will not be treatable by other antibacterial drugs in the future.
- Advise patient not to chew or crush the tablet.
- Advise patients to split MINOLIRA tablet across the score line, if required depending on patient's body weight.

Manufactured by:
Dr. Reddy's Laboratories Limited
FTO-SEZ-Process-Unit-01
Survey No: 57 to 59, 60, 52 & 72
Sector No: 9 to14 & 17 to 20, Devunipalavalasa Village
Ranasthalam Mandal
Srikakulam District
Andhra Pradesh, India

Manufactured for:
EPI Health, LLC
134 Columbus St.
Charleston, SC 29403, USA

MIN-PI-0618
150073673

PATIENT INFORMATION MINOLIRA (min-oh-li'-rah) (minocycline hydrochloride) extended-release tablets

WHAT IS MINOLIRA?

MINOLIRA is prescription medicine used to treat only pimples and red bumps (non-nodular inflammatory lesions) that happen with moderate to severe acne vulgaris in people 12 years and older.

MINOLIRA should not be used for the treatment of infections.

It is not known if MINOLIRA is safe and effective in children under the age of 12 years.

Who should not take MINOLIRA?

- Do not take MINOLIRA if you are allergic to medicines in the tetracycline class. Ask your healthcare provider or pharmacist for a list of these medicines if you are not sure.

Before you take MINOLIRA, tell your healthcare provider about all of your medical conditions, including if you:

- have kidney problems
- have liver problems
- have diarrhea or watery stools
- have vision problems.
- are pregnant or plan to become pregnant. MINOLIRA may harm your unborn baby. Taking MINOLIRA while you are pregnant may cause serious side effects on the growth of bone and teeth of your baby. Stop taking MINOLIRA and call your healthcare provider right away if you become pregnant during treatment with MINOLIRA.
- are breastfeeding or plan to breastfeed. MINOLIRA can pass into your breast milk and may harm your baby. You should not breastfeed during treatment with MINOLIRA.

Tell your healthcare provider about all the other medicines you take, including prescription and over-the-counter medicines, vitamins, and herbal supplements. MINOLIRA and other medicines may affect each other causing serious side effects.

Especially tell your healthcare provider if you take:

- birth control pills. MINOLIRA may reduce the effectiveness of certain birth control pills. You could become pregnant. You should use a second form of birth control during treatment with MINOLIRA. Talk to your healthcare provider about what types of birth control you can use to prevent pregnancy during treatment with MINOLIRA.
- a medicine taken by mouth that contains isotretinoin.

How should I take MINOLIRA?

See the detailed "Instructions for Use" that comes with MINOLIRA for information about breaking your MINOLIRA extended-release tablets.

- Take MINOLIRA exactly as your healthcare provider tells you.
- Your healthcare provider will tell you how much MINOLIRA to take and if you will need to break your MINOLIRA extended-release tablets based on your weight. MINOLIRA comes in 2 strengths:
  - 105 mg extended-release tablets
  - 135 mg extended-release tablets
- Do not miss your dose of MINOLIRA. Missing doses or not taking all doses of MINOLIRA may:
  - make the treatment not work as well
  - increase the chance that the bacteria will become resistant to MINOLIRA
- Take MINOLIRA with or without food. Taking MINOLIRA with food may lower your risk of getting irritation or ulcers in your esophagus. Your esophagus is the tube that connects your mouth to your stomach.
- Do not crush or chew MINOLIRA tablets.
- If you take too much MINOLIRA, call your healthcare provider right away or go to the nearest hospital emergency room.

What should I avoid during treatment with MINOLIRA?

- Avoid sunlight or artificial sunlight, such as sunlamps or tanning beds. You could get severe sunburn. Use sunscreen and wear loose-fitting clothes that cover your skin while out in sunlight. Stop taking MINOLIRA if you get sunburn.
- You should not drive or operate dangerous machinery until you know how MINOLIRA affects you. MINOLIRA may cause you to feel dizzy or lightheaded, or have a spinning feeling (vertigo).

What are possible side effects of MINOLIRA?

MINOLIRA may cause serious side effects, including:

- Harm to an unborn baby. See "What should I tell my healthcare provider before taking MINOLIRA?"
- Permanent teeth discoloration. MINOLIRA may permanently turn a baby or child's teeth yellow-gray-brown during tooth development. You should not use MINOLIRA during tooth development. Tooth development happens in the second and third trimesters of pregnancy, and from birth to 8 years of age.
- Slow bone growth. MINOLIRA may slow bone growth in infants and children. Slow bone growth is reversible after stopping treatment with MINOLIRA.
- Diarrhea. Diarrhea can happen with most antibiotics, including MINOLIRA. This diarrhea may be caused by an infection (Clostridium difficile) in your intestines. Call your healthcare provider right away if you get watery or bloody stools.
- Liver problems. MINOLIRA can cause liver problems that may lead to death. Stop taking MINOLIRA and call your healthcare provider right away if you get any of the following signs or symptoms of liver problems:
  - loss of appetite
  - tiredness
  - diarrhea
  - yellowing of your skin or the whites of your eyes
  - bleeding more easily than normal
  - confusion
  - sleepiness
- Increased pressure around the brain (intracranial hypertension). This condition may lead to vision changes and permanent vision loss. You may be more likely to get intracranial hypertension if you are a female of childbearing potential and are overweight or have a history of intracranial hypertension. Stop taking MINOLIRA and tell your healthcare provider right away if you have blurred vision, double vision, vision loss, or headaches.
- Immune system reactions including a lupus-like syndrome, hepatitis, and inflammation of blood or lymph vessels (vasculitis). Call your healthcare provider right away if you get a fever, rash, joint pain, or body weakness.
- Serious skin or allergic reactions that may affect parts of your body such as your liver, lungs, kidneys and heart. Sometimes these can lead to death. Stop taking MINOLIRA and go to the nearest hospital emergency room right away if you have any of the following signs or symptoms:
  - skin rash, hives, sores in your mouth, or your skin blisters and peels
  - swelling of your face, eyes, lips, tongue, or throat
  - trouble swallowing or breathing
  - blood in your urine
  - fever, yellowing of the skin or the whites of your eyes, dark colored urine
  - pain on the right side of the stomach area (abdominal pain)
  - chest pain or abnormal heartbeats
  - swelling in your legs, ankles, and feet
  - darkening of your nails, skin, eyes, scars, teeth, and gums
  - Discoloration (hyperpigmentation). MINOLIRA can cause darkening of your skin, scars, teeth, gums, nails, and whites of your eyes.

The most common side effects of MINOLIRA include:

- headache
- tiredness
- dizziness
- itching

MINOLIRA may cause fertility problems in males. This may affect your ability to father a child. Talk to your healthcare provider if you have concerns about fertility.

Your healthcare provider may tell you to decrease your dose or completely stop taking MINOLIRA if you develop certain serious side effects during treatment with MINOLIRA.

Your healthcare provider may do blood tests to check you for side effects during treatment with MINOLIRA.

These are not all the side effects of MINOLIRA. Call your doctor for medical advice about side effects. You may report side effects to FDA at 1-800-FDA-1088. You may also report side effects to EPI Health, LLC at 1-800-499-4468.

How should I store MINOLIRA?

- Store MINOLIRA at room temperature between 68°F to 77°F (20°C to 25°C).
- Keep MINOLIRA in the container that it comes in and keep the container tightly closed.
- Keep MINOLIRA away from light and moisture.

Keep MINOLIRA and all medicines out of the reach of children. General information about the safe and effective use of MINOLIRA.

Medicines are sometimes prescribed for purposes other than those listed in the Patient Information leaflet. Do not use MINOLIRA for a condition for which it was not prescribed. Do not give MINOLIRA to other people, even if they have the same symptoms you have. It may harm them. You can ask your healthcare provider or pharmacist for information about MINOLIRA that is written for health professionals.

What are the ingredients in MINOLIRA?

Active ingredient: minocycline hydrochloride.

Inactive ingredients: ethyl cellulose, hypromellose, isopropyl alcohol, microcrystalline cellulose, polyethylene glycol 400, purified water, silicified microcrystalline cellulose, sodium stearyl fumarate, talc, triethyl citrate

Both 105 mg and 135 mg tablets also contain Opadry clear which contains hydroxyl propyl cellulose and hypromellose.

Manufactured for:
EPI Health, LLC
134 Columbus St.
Charleston, SC 29403, USA

Manufactured by:
Dr. Reddy's Laboratories Limited
FTO-SEZ, Process Unit-01,
Devunipalavalasa Village, Srikakulam (District),
Andhra Pradesh, India.
Pin-:532409

MINOLIRA is a registered trademark of EPI Health, LLC

Item No. MIN-PI-0618/150073673

Issued: 06/2018

INSTRUCTIONS FOR USE MINOLIRA (min-oh-li'-rah) (minocycline hydrochloride) extended-release tablets

Read this Instructions for Use before you start using MINOLIRA and each time you get a refill. There may be new information. This information does not take the place of talking to your healthcare provider about your medical condition or treatment.

Note:

- Your healthcare provider will tell you how much of MINOLIRA to take and if you will need to break MINOLIRA extended-release tablets based on your weight.
- MINOLIRA comes in 2 strengths:
  - 105 mg extended-release tablets
  - 135 mg extended-release tablets

The 105 mg MINOLIRA tablets:

- are marked with an "M" and "1" on one side and is separated by a scored line
- can be taken whole or may be broken at the scored line to provide two equal halves of 52.5 mg each

How to break your MINOLIRA tablets?

- Hold the tablet between your thumbs and index fingers close to the scored line.
- Apply enough pressure to break the tablet at the scored line.
- Do not break the MINOLIRA tablet in any other way.
  - 105 mg treatment (take whole tablet)

top view of whole tablet

side view of whole tablet

side view of whole tablet with thumbs and index fingers

  - 52.5 mg treatment (take one-half of the tablet)

side view of breaking a whole tablet with thumbs and index fingers

top view of a split tablet

side view of one-half tablet with a thumb and an index finger

The 135 mg MINOLIRA tablets:

- are marked with an "M" and "3" on one side and is separated by a scored line
- can be taken whole or may be broken at the scored line to provide two equal halves of 67.5 mg each

How to break your MINOLIRA tablets?

- Hold the tablet between your thumbs and index fingers close to the scored line.
- Apply enough pressure to break the tablet at the scored line.
- Do not break the MINOLIRA tablet in any other way.
  - 135 mg treatment (take whole tablet)

top view of whole tablet

side view of whole tablet

side view of whole tablet with thumbs and index fingers

  - 67.5 mg treatment (take one-half of the tablet)

side view of breaking a whole tablet with thumbs and index fingers

top view of a split tablet

side view of one-half tablet with a thumb and an index finger

How should I store MINOLIRA?

- Store MINOLIRA at room temperature between 68°F to 77°F (20°C to 25°C).
- Keep MINOLIRA in the container that it comes in and keep the container tightly closed.
- Keep MINOLIRA away from light and moisture.

Keep MINOLIRA and all medicines out of the reach of children.

This Instructions for Use has been approved by the U.S. Food and Drug Administration.

Manufactured for:
EPI Health, LLC
134 Columbus St.
Charleston, SC 29403, USA

Manufactured by:
Dr. Reddy's Laboratories Limited
FTO-SEZ, Process Unit-01,
Devunipalavalasa Village, Srikakulam (District),
Andhra Pradesh, India.
Pin-:532409

MINOLIRA is a registered trademark of EPI Health, LLC

Item No. MIN-PI-0618/150073673

Issued: 06/2018

PRINCIPAL DISPLAY PANEL - 135 mg Tablet Bottle Label

NDC 71403-102-30
Rx Only

minolira™
(minocycline hydrochloride)
extended-release tablets

135 mg*

*Each tablet contains 135 mg of minocycline
(33.75 mg as immediate release beads and
101.25 mg as extended release beads), equivalent
to 145.8 mg of minocycline hydrochloride.

30 Tablets

EPIHEALTH
Advancing Dermatology

PRINCIPAL DISPLAY PANEL - 105 mg Tablet Bottle Label

NDC 71403-101-30
Rx Only

minolira™
(minocycline hydrochloride)
extended-release tablets

105 mg*

*Each tablet contains 105 mg of minocycline
(26.25 mg as immediate release beads and 78.75
mg as extended release beads), equivalent to
113.4 mg of minocycline hydrochloride.

30 Tablets

EPIHEALTH
Advancing Dermatology